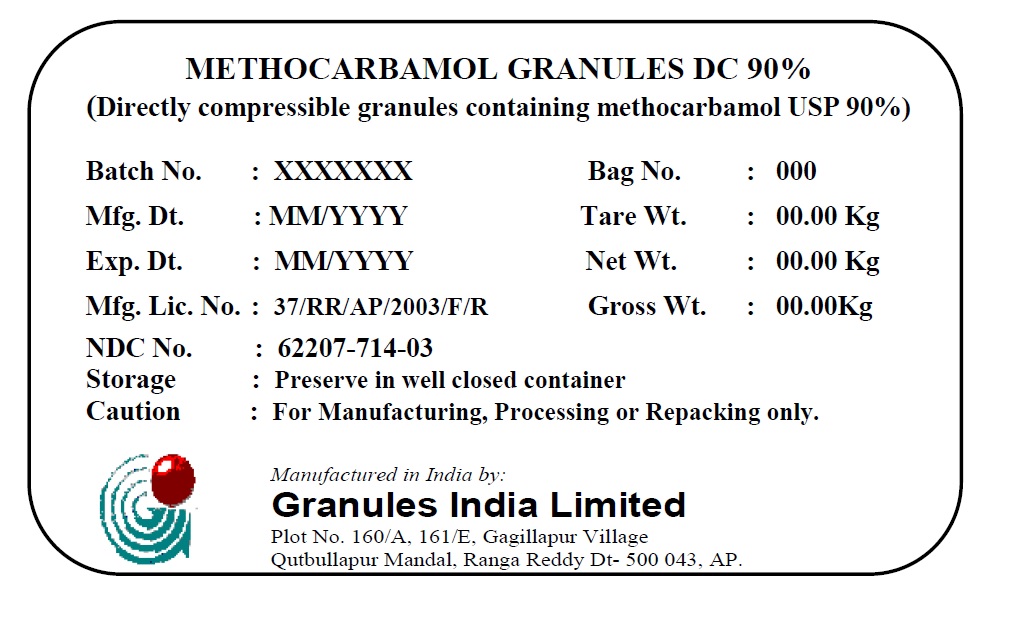 DRUG LABEL: Methocarbamol Granules DC 90%
NDC: 62207-714 | Form: POWDER
Manufacturer: Granules India Limited
Category: other | Type: BULK INGREDIENT
Date: 20230227

ACTIVE INGREDIENTS: METHOCARBAMOL 90 mg/100 1
INACTIVE INGREDIENTS: POVIDONE K30; STARCH, CORN; STEARIC ACID; SODIUM STARCH GLYCOLATE TYPE A CORN; SODIUM LAURYL SULFATE; SILICON DIOXIDE

Methocarbamol Granules DC 90%

(Directly compressible granules containing Methocarbamol DC - 90%)

DESCRIPTION

SPECIMEN LABEL

Batch No.: XXX Drum No.: XXX

Mfg. Dt.: XXX Tare Wt.: XXX

Exp. Dt.: XXX Net Wt.: XXX

Mfg. Lic. No.: XXX Gross Wt.: XXX

NDC No. 62207-714

HOW SUPPLIED

Storage: Preserve in well closed container

Caution For Manufacturing, Processing, or Repacking only.

Manufactured in India by: Granules India Limited Plot No. 160/A, 161/E, Gagillapur Village Qutbullapur Mandal, Ranga Reddy Dt – 500 043, AP.